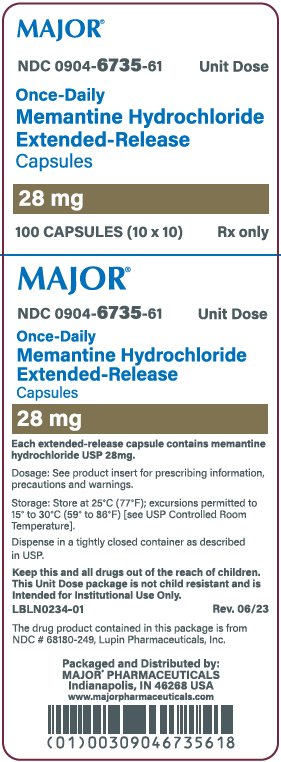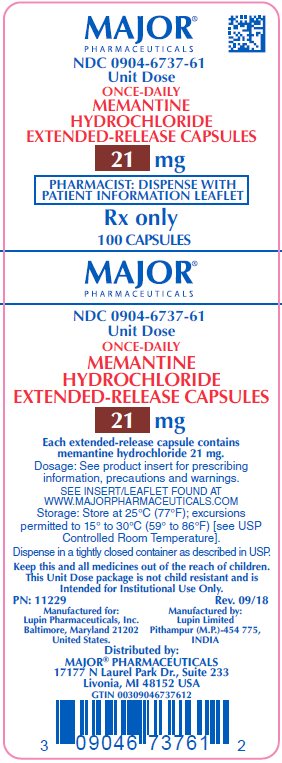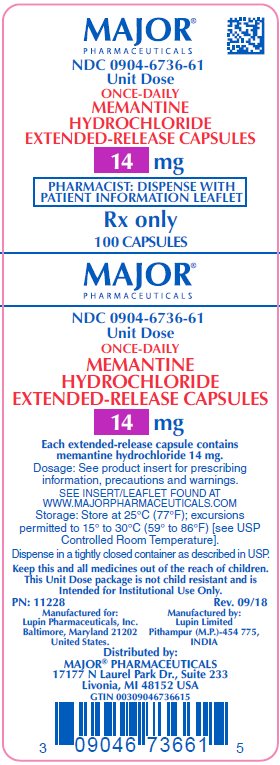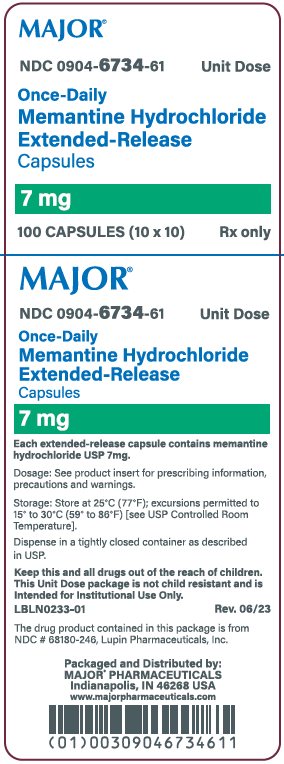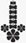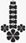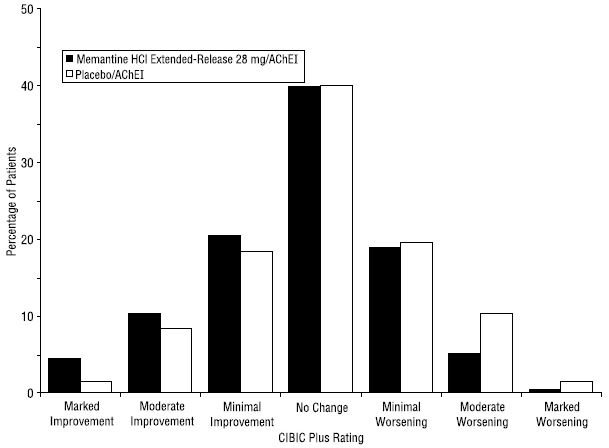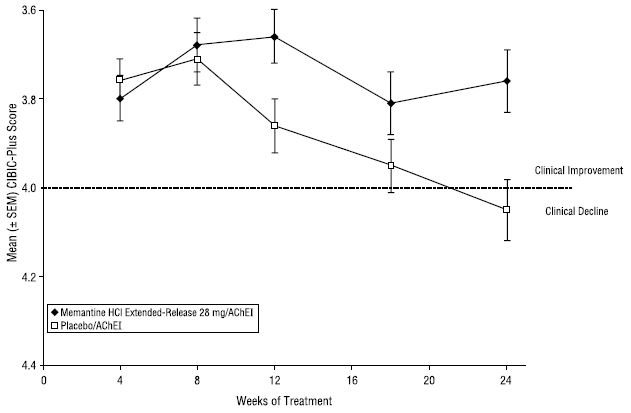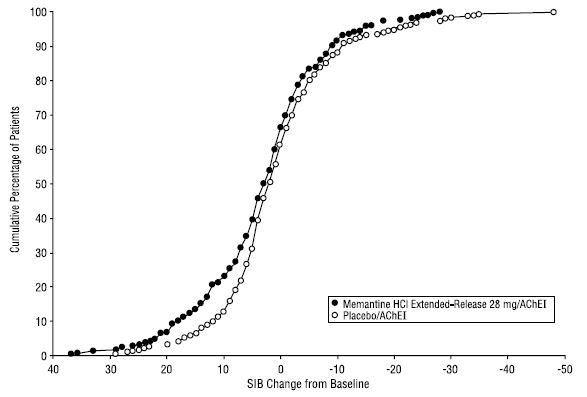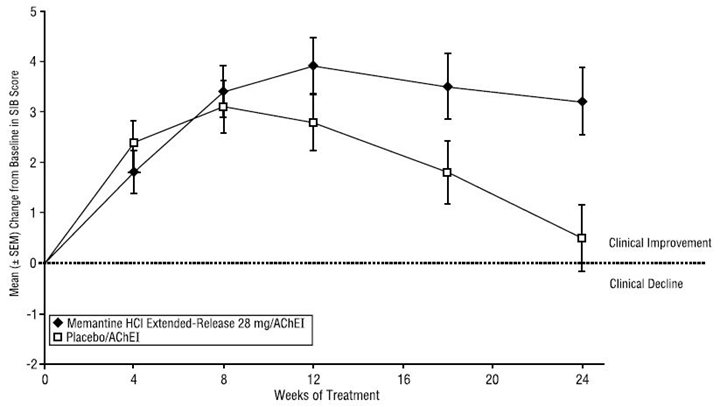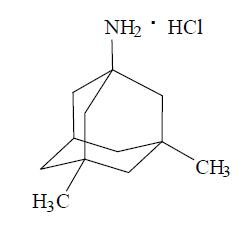 DRUG LABEL: memantine hydrochloride
NDC: 0904-6734 | Form: CAPSULE, EXTENDED RELEASE
Manufacturer: Major Pharmaceuticals
Category: prescription | Type: HUMAN PRESCRIPTION DRUG LABEL
Date: 20260107

ACTIVE INGREDIENTS: MEMANTINE HYDROCHLORIDE 7 mg/1 1
INACTIVE INGREDIENTS: ETHYLCELLULOSE, UNSPECIFIED; GELATIN, UNSPECIFIED; HYPROMELLOSE, UNSPECIFIED; STARCH, CORN; SUCROSE; TALC; TITANIUM DIOXIDE; TRIETHYL CITRATE; D&C YELLOW NO. 10; FD&C RED NO. 40; FERROSOFERRIC OXIDE; POTASSIUM HYDROXIDE; PROPYLENE GLYCOL; SHELLAC

HIGHLIGHTS OF PRESCRIBING INFORMATION

These highlights do not include all the information needed to use MEMANTINE HYDROCHLORIDE EXTENDED-RELEASE CAPSULES safely and effectively. See full prescribing information for MEMANTINE HYDROCHLORIDE EXTENDED-RELEASE CAPSULES.
MEMANTINE HYDROCHLORIDE extended-release capsules, for oral use
Initial U.S. Approval: 2003

1 INDICATIONS AND USAGE

Memantine hydrochloride extended-release capsules are a N-methyl-D-aspartate (NMDA) receptor antagonist indicated for the treatment of moderate to severe dementia of the Alzheimer's type. (1)

2 DOSAGE AND ADMINISTRATION

- The recommended starting dose of memantine hydrochloride extended-release capsules is 7 mg once daily; the dose should be increased in 7 mg increments to the recommended maintenance dose of 28 mg once daily; the minimum recommended interval between dose increases is one week. (2.1)
- Patients with severe renal impairment: the recommended maintenance dose of memantine hydrochloride extended-release capsules is 14 mg once daily. (2.3)

3 DOSAGE FORMS AND STRENGTHS

Memantine hydrochloride extended-release capsule is available as an extended-release capsule in the following strengths: 7 mg, 14 mg, 21 mg, 28 mg (3)

4 CONTRAINDICATIONS

Memantine hydrochloride extended-release is contraindicated in patients with known hypersensitivity to memantine hydrochloride or to any excipients used in the formulation. (4)

5 WARNINGS AND PRECAUTIONS

Conditions that raise urine pH may decrease the urinary elimination of memantine resulting in increased plasma levels of memantine. (5.1,7.1)

6 ADVERSE REACTIONS

The most commonly observed adverse reactions occurring at a frequency of at least 5% and greater than placebo with administration of memantine hydrochloride extended-release 28 mg/day were headache, diarrhea and dizziness. (6.1)

To report SUSPECTED ADVERSE REACTIONS, contact Lupin Pharmaceuticals, Inc. at 1-800-399-2561 or FDA at 1-800-FDA-1088 or www.fda.gov/medwatch.

FULL PRESCRIBING INFORMATION

1 INDICATIONS AND USAGE

Memantine hydrochloride extended-release capsules are indicated for the treatment of moderate to severe dementia of the Alzheimer's type.

2 DOSAGE AND ADMINISTRATION

2.1 Recommended Dosing

The dosage of memantine hydrochloride extended-release capsule shown to be effective in a controlled clinical trial is 28 mg once daily.

The recommended starting dose of memantine hydrochloride extended-release capsule is 7 mg once daily. The dose should be increased in 7 mg increments to the recommended maintenance dose of 28 mg once daily. The minimum recommended interval between dose increases is one week. The dose should only be increased if the previous dose has been well tolerated. The maximum recommended dose is 28 mg once daily.

Memantine hydrochloride extended-release capsules can be taken with or without food. Memantine hydrochloride extended-release capsules can be taken intact or may be opened, sprinkled on applesauce, and thereby swallowed. The entire contents of each memantine hydrochloride extended-release capsule should be consumed; the dose should not be divided.

Except when opened and sprinkled on applesauce, as described above, memantine hydrochloride extended-release capsules should be swallowed whole. Memantine hydrochloride extended-release capsules should not be divided, chewed, or crushed.

If a patient misses a single dose of memantine hydrochloride extended-release capsules, that patient should not double up on the next dose. The next dose should be taken as scheduled. If a patient fails to take memantine hydrochloride extended-release capsules for several days, dosing may need to be resumed at lower doses and retitrated as described above.

2.2 Switching from Memantine hydrochloride Tablets to Memantine hydrochloride Extended-Release Capsules

Patients treated with memantine hydrochloride tablets may be switched to memantine hydrochloride extended-release capsules as follows:

It is recommended that a patient who is on a regimen of 10 mg twice daily of memantine hydrochloride tablets be switched to memantine hydrochloride extended-release 28 mg once daily capsules the day following the last dose of 10 mg memantine hydrochloride tablets. There is no study addressing the comparative efficacy of these 2 regimens.

In a patient with severe renal impairment, it is recommended that a patient who is on a regimen of 5 mg twice daily of memantine hydrochloride tablets be switched to memantine hydrochloride extended-release 14 mg once daily capsules the day following the last dose of 5 mg memantine hydrochloride tablets.

2.3 Dosing in Patients with Renal Impairment

In patients with severe renal impairment (creatinine clearance of 5 to 29 mL/min, based on the Cockcroft-Gault equation), the recommended maintenance dose (and maximum recommended dose) is 14 mg/day [see CLINICAL PHARMACOLOGY (12.3)].

3 DOSAGE FORMS AND STRENGTHS

Each extended-release capsule contains 7 mg, 14 mg, 21 mg, or 28 mg of memantine hydrochloride USP.

● 7 mg: Size '4' hard gelatin yellow capsule with yellow opaque cap and yellow opaque body, with black imprint "LU" on cap and "O61" on body.

● 14 mg: Size '4' hard gelatin capsule with yellow opaque cap and dark green opaque body, with black imprint "LU" on cap and "O62" on body.

● 21 mg: Size '4' hard gelatin capsule with white opaque cap and dark green opaque body, with black imprint "LU" on cap and "O63" on body.

● 28 mg: Size '3' hard gelatin dark green capsule with black imprint "LU" on cap and "O64" on body.

4 CONTRAINDICATIONS

Memantine hydrochloride extended-release is contraindicated in patients with known hypersensitivity to memantine hydrochloride or to any excipients used in the formulation.

5 WARNINGS AND PRECAUTIONS

5.1 Genitourinary Conditions

Conditions that raise urine pH may decrease the urinary elimination of memantine resulting in increased plasma levels of memantine [see DRUG INTERACTIONS (7.1)].

6 ADVERSE REACTIONS

6.1 Clinical Trials Experience

Memantine hydrochloride extended-release was evaluated in a double-blind placebo-controlled trial in which a total of 676 patients with moderate to severe dementia of the Alzheimer's type (341 patients on memantine hydrochloride extended-release 28 mg/day and 335 patients on placebo) were treated for up to 24 weeks.

Because clinical trials are conducted under widely varying conditions, adverse reaction rates observed in the clinical trials of a drug cannot be directly compared to rates in the clinical trials of another drug and may not reflect the rates observed in practice.

Adverse Reactions Leading to Discontinuation

In the placebo-controlled clinical trial of memantine hydrochloride extended-release, the proportion of patients in the memantine hydrochloride extended-release capsules group and the placebo group who discontinued treatment due to adverse reactions was 10% and 6%, respectively. The most common adverse reaction that led to treatment discontinuation in the memantine hydrochloride extended-release group was dizziness, at a rate of 1.5%.

Most Common Adverse Reactions

The most commonly observed adverse reactions seen in patients administered memantine hydrochloride extended-release in the controlled clinical trial, defined as those occurring at a frequency of at least 5% in the memantine hydrochloride extended-release group and at a frequency higher than placebo, were headache, diarrhea and dizziness.

Table 1 lists adverse reactions that were observed at an incidence of ≥ 2% in the memantine hydrochloride extended-release group and occurred at a rate greater than placebo.

Table 1: Adverse Reactions Observed with a Frequency of ≥ 2% in the memantine hydrochloride extended-release Group and at a Rate Greater than Placebo
Adverse Reaction | Placebo (n = 335) % | Memantine Hydrochloride Extended-Release 28 mg (n = 341) %
Gastrointestinal Disorders
Diarrhea | 4 | 5
Constipation | 1 | 3
Abdominal pain | 1 | 2
Vomiting | 1 | 2
Infections and Infestations
Influenza | 3 | 4
Investigations
Weight, increased | 1 | 3
Musculoskeletal and Connective Tissue Disorders
Back pain | 1 | 3
Nervous System Disorders
Headache | 5 | 6
Dizziness | 1 | 5
Somnolence | 1 | 3
Psychiatric Disorders
Anxiety | 3 | 4
Depression | 1 | 3
Aggression | 1 | 2
Renal and Urinary Disorders
Urinary incontinence | 1 | 2
Vascular Disorders
Hypertension | 2 | 4
Hypotension | 1 | 2

Seizure

Memantine has not been systematically evaluated in patients with a seizure disorder. In clinical trials of memantine, seizures occurred in 0.3% of patients treated with memantine and 0.6% of patients treated with placebo.

6.2 Postmarketing Experience

The following adverse reactions have been identified during post-approval use of memantine.

Because these reactions are reported voluntarily from a population of uncertain size, it is not always possible to reliably estimate their frequency or establish a causal relationship to drug exposure. These reactions include:

Blood and Lymphatic System Disorders: agranulocytosis, leukopenia (including neutropenia), pancytopenia, thrombocytopenia, thrombotic thrombocytopenic purpura.

Cardiac Disorders: cardiac failure congestive.

Gastrointestinal Disorders: pancreatitis.

Hepatobiliary Disorders: hepatitis.

Psychiatric Disorders: suicidal ideation.

Renal and Urinary Disorders: acute renal failure (including increased creatinine and renal insufficiency).

Skin Disorders: Stevens Johnson syndrome.

7 DRUG INTERACTIONS

7.1 Drugs That Make Urine Alkaline

The clearance of memantine was reduced by about 80% under alkaline urine conditions at pH 8. Therefore, alterations of urine pH towards the alkaline condition may lead to an accumulation of the drug with a possible increase in adverse effects. Urine pH is altered by diet, drugs (e.g. carbonic anhydrase inhibitors, sodium bicarbonate) and clinical state of the patient (e.g. renal tubular acidosis or severe infections of the urinary tract). Hence, memantine should be used with caution under these conditions.

7.2 Use with Other N-methyl-D-aspartate (NMDA) Antagonists

The combined use of memantine hydrochloride extended-release with other NMDA antagonists (amantadine, ketamine, and dextromethorphan) has not been systematically evaluated and such use should be approached with caution.

8 USE IN SPECIFIC POPULATIONS

8.1 Pregnancy

Risk Summary

There are no adequate data on the developmental risk associated with the use of memantine hydrochloride extended release in pregnant women.

Adverse developmental effects (decreased body weight and skeletal ossification) were observed in the offspring of rats administered memantine during pregnancy at doses associated with minimal maternal toxicity. These doses are higher than those used in humans at the maximum recommended daily dose of memantine hydrochloride extended release [see Data].

In the U.S. general population, the estimated background risk of major birth defects and miscarriage in clinically recognized pregnancies is 2 to 4% and 15 to 20%, respectively. The background risk of major birth defects and miscarriage for the indicated population is unknown.

Data

Animal Data

Oral administration of memantine (0, 2, 6, or 18 mg/kg/day) to rats during the period of organogenesis resulted in decreased skeletal ossification in fetuses at the highest dose tested. The higher no-effect dose for adverse developmental effects (6 mg/kg) is 2 times the maximum recommended human daily dose (MRHD) of memantine hydrochloride extended release (28 mg) on a body surface area (mg/m^2) basis.

Oral administration of memantine to rabbits (0, 3, 10, or 30 mg/kg/day) during the period of organogenesis resulted in no adverse developmental effects. The highest dose tested is approximately 20 times the MRHD of memantine hydrochloride extended release on a mg/m^2 basis.

In rats, memantine (0, 2, 6, or 18 mg/kg/day) was administered orally prior to and throughout mating and, in females, through the period of organogenesis or continuing throughout lactation to weaning. Decreased skeletal ossification in fetuses and decreased body weight in pups were observed at the highest dose tested. The higher no-effect dose for adverse developmental effects (6 mg/kg/day) is 2 times the MRHD of memantine hydrochloride extended release on a mg/m^2 basis.

Oral administration of memantine (0, 2, 6, or 18 mg/kg/day) to rats from late gestation throughout lactation to weaning, resulted in decreased pup weights at the highest dose tested. The higher no-effect dose (6 mg/kg/day) is approximately 2 times the MRHD of memantine hydrochloride extended release on a mg/m^2 basis.

8.2 Lactation

Risk Summary

There are no data on the presence of memantine in human milk, the effects on the breastfed infant, or the effects of memantine hydrochloride extended release on milk production.

The developmental and health benefits of breastfeeding should be considered along with the mother's clinical need for memantine hydrochloride extended release and any potential adverse effects on the breastfed infant from memantine hydrochloride extended release or from the underlying maternal condition.

8.4 Pediatric Use

Safety and effectiveness in pediatric patients have not been established.

Memantine failed to demonstrate efficacy in two 12-week controlled clinical studies of 578 pediatric patients aged 6 to 12 years with autism spectrum disorders (ASD), including autism, Asperger's disorder and Pervasive Development Disorder -Not Otherwise Specified (PDD-NOS). Memantine has not been studied in pediatric patients under 6 years of age or over 12 years of age. Memantine treatment was initiated at 3 mg/day and the dose was escalated to the target dose (weight-based) by week 6. Oral doses of memantine 3, 6, 9, or 15 mg extended-release capsules were administered once daily to patients with weights < 20 kg, 20 to 39 kg, 40 to 59 kg and ≥ 60 kg, respectively.

In a randomized, 12-week double-blind, placebo-controlled parallel study (Study A) in patients with autism, there was no statistically significant difference in the Social Responsiveness Scale (SRS) total raw score between patients randomized to memantine (n=54) and those randomized to placebo (n=53). In a 12-week responder-enriched randomized withdrawal study (Study B) in 471 patients with ASD, there was no statistically significant difference in the loss of therapeutic response rates between patients randomized to remain on full-dose memantine (n=153) and those randomized to switch to placebo (n=158).

The overall safety profile of memantine in pediatric patients was generally consistent with the known safety profile in adults [see Adverse Reactions (6.1)].

In Study A, the adverse reactions in the memantine group (n=56) that were reported in at least 5% of patients and at least twice the frequency of the placebo group (N=58) are listed in Table 2.

Table 2: Study A Commonly Reported Adverse Reactions with a Frequency ≥ 5% and Twice That of Placebo
Adverse Reaction | Memantine N=56 | Placebo N=58
Cough | 8.9% | 3.4%
Influenza | 7.1% | 3.4%
Rhinorrhea | 5.4% | 0%
Agitation | 5.4% | 1.7%
Discontinuations due to Adverse Reactions [Reported adverse reactions leading to discontinuation in more than one patient in either treatment group.]
Aggression | 3.6% | 1.7%
Irritability | 1.8% | 3.4%

The adverse reactions that were reported in at least 5% of patients in the 12 to 48 week open-label study to identify responders to enroll in Study B are listed in Table 3:

Table 3: 12 to 48 Week Open Label Lead-In study to Study B Commonly Reported Adverse Reactions with a Frequency ≥ 5%
Adverse Reaction | Memantine N=903
Headache | 8%
Nasopharyngitis | 6.3%
Pyrexia | 5.8%
Irritability | 5.4%
Discontinuations due to Adverse Reactions [At least 1% incidence of adverse reactions leading to premature discontinuation.]
Irritability | 1.2%
Aggression | 1%

In the randomized withdrawal study (Study B), the adverse reaction in patients randomized to placebo (n=160) and reported in at least 5% of patients and twice that of the full-dose memantine treatment group (n=157) was irritability (5% vs 2.5%).

Juvenile Animal Study

In a juvenile animal study, male and female juvenile rats were administered memantine (15, 30, and 45 mg/kg/day) starting on postnatal day (PND) 14 through PND 70. Body weights were reduced at 45 mg/kg/day. Delays in sexual maturation were noted in male and female rats at doses ≥ 30 mg/kg/day. Memantine induced neuronal lesions in several areas of the brain on PND 15 and 17 at doses ≥ 30 mg/kg/day. Behavioral toxicity (decrease percent of auditory startle habituation) was noted for animals in the 45 mg/kg/day dose group. The 15 mg/kg/day dose was considered the No-Observed-Adverse-Effect-Level (NOAEL) for this study.

In a second juvenile rat toxicity study, male and female juvenile rats were administered memantine (1, 3, 8, 15, 30, and 45 mg/kg/day) starting on postnatal day (PND) 7 through PND 70. Due to early memantine-related mortality, the 30 and 45 mg/kg/day dose groups were terminated without further evaluation. Memantine induced apoptosis or neuronal degeneration in several areas of the brain on PND 8, 10, and 17 at a dose of 15 mg/kg/day. The NOAEL for apoptosis and neuronal degeneration was 8 mg/kg/day. Behavioral toxicity (effects on motor activity, auditory startle habituation, and learning and memory) was noted at doses ≥ 3 mg/kg/day during treatment, but was not seen after drug discontinuation. Therefore, the 1 mg/kg/day dose was considered the NOAEL for the neurobehavioral effect in this study.

8.5 Geriatric Use

The majority of people with Alzheimer's disease are 65 years of age and older. In the clinical study of memantine hydrochloride extended-release, the mean age of patients was approximately 77 years; over 91% of patients were 65 years and older, 67% were 75 years and older, and 14% were at or above 85 years of age. The efficacy and safety data presented in the clinical trial sections were obtained from these patients. There were no clinically meaningful differences in most adverse reactions reported by patient groups ≥ 65 years old and < 65 years old.

8.6 Renal Impairment

No dosage adjustment is needed in patients with mild or moderate renal impairment. A dosage reduction is recommended in patients with severe renal impairment [see Dosage and Administration (2.3) and Clinical Pharmacology (12.3)].

8.7 Hepatic Impairment

No dosage adjustment is needed in patients with mild or moderate hepatic impairment. Memantine hydrochloride extended-release was not studied in patients with severe hepatic impairment [see Clinical Pharmacology (12.3)].

10 OVERDOSAGE

Signs and symptoms most often accompanying overdosage with other formulations of memantine in clinical trials and from worldwide marketing experience, alone or in combination with other drugs and/or alcohol, include agitation, asthenia, bradycardia, confusion, coma, dizziness, ECG changes, increased blood pressure, lethargy, loss of consciousness, psychosis, restlessness, slowed movement, somnolence, stupor, unsteady gait, visual hallucinations, vertigo, vomiting, and weakness. The largest known ingestion of memantine worldwide was 2 grams in a patient who took memantine in conjunction with unspecified antidiabetic medications. This patient experienced coma, diplopia, and agitation, but subsequently recovered.

One patient participating in a memantine hydrochloride extended-release clinical trial unintentionally took 112 mg of memantine hydrochloride extended-release daily for 31 days and experienced an elevated serum uric acid, elevated serum alkaline phosphatase, and low platelet count.

Fatal outcome has been very rarely reported with memantine, and the relationship to memantine was unclear.

Because strategies for the management of overdose are continually evolving, it is advisable to contact a poison control center to determine the latest recommendations for the management of an overdose of any drug. As in any cases of overdose, general supportive measures should be utilized, and treatment should be symptomatic.

Elimination of memantine can be enhanced by acidification of urine.

11 DESCRIPTION

Memantine hydrochloride extended-release is an orally active NMDA receptor antagonist. The chemical name for memantine hydrochloride is 1-amino-3,5-dimethyladamantane hydrochloride with the following structural formula:

The molecular formula is C12H21N•HCl and the molecular weight is 215.76. Memantine hydrochloride occurs as a white to off-white powder and is soluble in water.

Memantine hydrochloride extended-release capsules are supplied for oral administration as 7 mg, 14 mg, 21 mg, and 28 mg capsules. Each capsule contains extended-release pellets with the labeled amount of memantine hydrochloride USP and the following inactive ingredients: ethyl cellulose, gelatin, hypromellose, maize starch, sucrose, talc, titanium dioxide and triethyl citrate in hard gelatin capsules. Additionally, 7 mg strength capsules contain D&C Yellow #10 and FD&C Red #40; 14 mg strength capsules contain D&C Yellow #10, FD&C Blue #1, FD&C Red #40 and iron oxide yellow; 21 mg and 28 mg strength capsules contain FD&C Blue #1 and iron oxide yellow. The capsules are printed with edible ink containing black iron oxide, potassium hydroxide, propylene glycol and shellac.

12 CLINICAL PHARMACOLOGY

12.1 Mechanism of Action

Persistent activation of central nervous system N-methyl-D-aspartate (NMDA) receptors by the excitatory amino acid glutamate has been hypothesized to contribute to the symptomatology of Alzheimer's disease. Memantine is postulated to exert its therapeutic effect through its action as a low to moderate affinity uncompetitive (open-channel) NMDA receptor antagonist which binds preferentially to the NMDA receptor-operated cation channels. There is no evidence that memantine prevents or slows neurodegeneration in patients with Alzheimer's disease.

12.2 Pharmacodynamics

Memantine showed low to negligible affinity for GABA, benzodiazepine, dopamine, adrenergic, histamine and glycine receptors and for voltage-dependent Ca^2+, Na^+, or K^+channels. Memantine also showed antagonistic effects at the 5HT3 receptor with a potency similar to that for the NMDA receptor and blocked nicotinic acetylcholine receptors with one-sixth to one-tenth the potency.

In vitro studies have shown that memantine does not affect the reversible inhibition of acetylcholinesterase by donepezil, galantamine, or tacrine.

12.3 Pharmacokinetics

Memantine is well absorbed after oral administration and has linear pharmacokinetics over the therapeutic dose range. It is excreted predominantly unchanged in urine and has a terminal elimination half-life of about 60 to 80 hours. In a study comparing 28 mg once daily memantine hydrochloride extended-release to 10 mg twice daily memantine hydrochloride tablets, the Cmax and AUC0-24 values were 48% and 33% higher for the XR dosage regimen, respectively.

Absorption

After multiple dose administration of memantine hydrochloride extended-release, memantine peak concentrations occur around 9 to 12 hours post-dose. There is no difference in the absorption of memantine hydrochloride extended-release when the capsule is taken intact or when the contents are sprinkled on applesauce.

There is no difference in memantine exposure, based on Cmax or AUC, for memantine hydrochloride extended-release whether that drug product is administered with food or on an empty stomach. However, peak plasma concentrations are achieved about 18 hours after administration with food versus approximately 25 hours after administration on an empty stomach.

Distribution

The mean volume of distribution of memantine is 9 to 11 L/kg and the plasma protein binding is low (45%).

Elimination

Metabolism

Memantine undergoes partial hepatic metabolism. The hepatic microsomal CYP450 enzyme system does not play a significant role in the metabolism of memantine.

Excretion

Memantine is excreted predominantly unchanged in the urine and has a terminal elimination half-life of about 60 to 80 hours. About 48% of administered drug is excreted unchanged in urine; the remainder is converted primarily to three polar metabolites which possess minimal NMDA receptor antagonistic activity: the N-glucuronide conjugate, 6-hydroxy memantine, and 1-nitroso-deaminated memantine. A total of 74% of the administered dose is excreted as the sum of the parent drug and the N-glucuronide conjugate. Renal clearance involves active tubular secretion moderated by pH dependent tubular reabsorption.

Specific Populations

Elderly

The pharmacokinetics of memantine in young and elderly subjects are similar.

Gender

Following multiple dose administration of memantine hydrochloride 20 mg daily, females had about 45% higher exposure than males, but there was no difference in exposure when body weight was taken into account.

Renal Impairment

Memantine pharmacokinetics were evaluated following single oral administration of 20 mg memantine hydrochloride in 8 subjects with mild renal impairment (creatinine clearance, CLcr, > 50 to 80 mL/min), 8 subjects with moderate renal impairment (CLcr 30 to 49 mL/min), 7 subjects with severe renal impairment (CLcr 5 to 29 mL/min) and 8 healthy subjects (CLcr > 80 mL/min) matched as closely as possible by age, weight and gender to the subjects with renal impairment. Mean AUC0-∞ increased by 4%, 60%, and 115% in subjects with mild, moderate, and severe renal impairment, respectively, compared to healthy subjects. The terminal elimination half-life increased by 18%, 41%, and 95% in subjects with mild, moderate, and severe renal impairment, respectively, compared to healthy subjects.

Hepatic Impairment

Memantine pharmacokinetics were evaluated following the administration of single oral doses of 20 mg in 8 subjects with moderate hepatic impairment (Child-Pugh Class B, score 7 to 9) and 8 subjects who were age-, gender-, and weight-matched to the hepatically impaired subjects. There was no change in memantine exposure (based on Cmax and AUC) in subjects with moderate hepatic impairment as compared with healthy subjects. However, terminal elimination half-life increased by about 16% in subjects with moderate hepatic impairment as compared with healthy subjects.

Drug-Drug Interactions

Use with Cholinesterase Inhibitors

Coadministration of memantine with the AChE inhibitor donepezil did not affect the pharmacokinetics of either compound. Furthermore, memantine did not affect AChE inhibition by donepezil. In a 24-week controlled clinical study in patients with moderate to severe Alzheimer's disease, the adverse reaction profile observed with a combination of memantine immediate-release and donepezil was similar to that of donepezil alone.

Effect of Memantine on the Metabolism of Other Drugs

In vitro studies conducted with marker substrates of CYP450 enzymes (CYP1A2, -2A6, 2C9, -2D6, -2E1, -3A4) showed minimal inhibition of these enzymes by memantine. In addition, in vitro studies indicate that at concentrations exceeding those associated with efficacy, memantine does not induce the cytochrome P450 isozymes CYP1A2, -2C9, 2E1 and -3A4/5. No pharmacokinetic interactions with drugs metabolized by these enzymes are expected.

Pharmacokinetic studies evaluated the potential of memantine for interaction with warfarin and bupropion. Memantine did not affect the pharmacokinetics of the CYP2B6 substrate bupropion or its metabolite hydroxybupropion. Furthermore, memantine did not affect the pharmacokinetics or pharmacodynamics of warfarin as assessed by the prothrombin INR.

Effect of Other Drugs on Memantine

Memantine is predominantly renally eliminated, and drugs that are substrates and/or inhibitors of the CYP450 system are not expected to alter the metabolism of memantine.

Drugs Eliminated via Renal Mechanisms

Because memantine is eliminated in part by tubular secretion, coadministration of drugs that use the same renal cationic system, including hydrochlorothiazide (HCTZ), triamterene (TA), metformin, cimetidine, ranitidine, quinidine, and nicotine, could potentially result in altered plasma levels of both agents. However, coadministration of memantine and HCTZ/TA did not affect the bioavailability of either memantine or TA, and the bioavailability of HCTZ decreased by 20%. In addition, coadministration of memantine with the antihyperglycemic drug Glucovance (glyburide and metformin hydrochloride) did not affect the pharmacokinetics of memantine, metformin and glyburide. Furthermore, memantine did not modify the serum glucose lowering effect of Glucovance, indicating the absence of a pharmacodynamic interaction.

Drugs Highly Bound to Plasma Proteins

Because the plasma protein binding of memantine is low (45%), an interaction with drugs that are highly bound to plasma proteins, such as warfarin and digoxin, is unlikely.

13 NONCLINICAL TOXICOLOGY

13.1 Carcinogenesis, Mutagenesis, Impairment of Fertility

Carcinogenesis

There was no evidence of carcinogenicity in a 113-week oral study in mice at doses up to 40 mg/kg/day (7 times the maximum recommended human dose [MRHD] on a mg/m^2 basis). There was also no evidence of carcinogenicity in rats orally dosed at up to 40 mg/kg/day for 71 weeks followed by 20 mg/kg/day (14 and 7 times the MRHD on a mg/m^2 basis, respectively) through 128 weeks.

Mutagenesis

Memantine produced no evidence of genotoxic potential when evaluated in the in vitro S. typhimurium or E. coli reverse mutation assay, an in vitro chromosomal aberration test in human lymphocytes, an in vivo cytogenetics assay for chromosome damage in rats, and the in vivo mouse micronucleus assay. The results were equivocal in an in vitro gene mutation assay using Chinese hamster V79 cells.

Impairment of Fertility

No impairment of fertility or reproductive performance was seen in rats administered up to 18 mg/kg/day (6 times the MRHD on a mg/m^2 basis) orally from 14 days prior to mating through gestation and lactation in females, or for 60 days prior to mating in males.

13.2 Animal Toxicology and /or Pharmacology

Memantine induced neuronal lesions (vacuolation and necrosis) in the multipolar and pyramidal cells in cortical layers III and IV of the posterior cingulate and retrosplenial neocortices in rats, similar to those which are known to occur in rodents administered other NMDA receptor antagonists. Lesions were seen after a single dose of memantine. In a study in which rats were given daily oral doses of memantine for 14 days, the no-effect dose for neuronal necrosis was 4 times the maximum recommended human dose (MRHD of 28 mg/day) on a mg/m^2 basis.

In acute and repeat-dose neurotoxicity studies in female rats, oral administration of memantine and donepezil in combination resulted in increased incidence, severity, and distribution of neurodegeneration compared with memantine alone. The no-effect levels of the combination were associated with clinically relevant plasma memantine and donepezil exposures.

The relevance of these findings to humans is unknown.

14 CLINICAL STUDIES

The effectiveness of memantine hydrochloride extended-release as a treatment for patients with moderate to severe Alzheimer's disease was based on the results of a double-blind, placebo-controlled trial.

24-week Study of Memantine Hydrochloride Extended-Release Capsules

This was a randomized double-blind clinical investigation in outpatients with moderate to severe Alzheimer's disease (diagnosed by DSM-IV criteria and NINCDS-ADRDA criteria for AD with a Mini Mental State Examination (MMSE) score ≥ 3 and ≤ 14 at Screening and Baseline) receiving acetylcholinesterase inhibitor (AChEI) therapy at a stable dose for 3 months prior to screening. The mean age of patients participating in this trial was 76.5 years with a range of 49 to 97 years. Approximately 72% of patients were female and 94% were Caucasian.

Study Outcome Measures

The effectiveness of memantine hydrochloride extended-release was evaluated in this study using the co-primary efficacy parameters of Severe Impairment Battery (SIB) and the Clinician's Interview-Based Impression of Change (CIBIC-Plus).

The ability of memantine hydrochloride extended-release to improve cognitive performance was assessed with the Severe Impairment Battery (SIB), a multi-item instrument that has been validated for the evaluation of cognitive function in patients with moderate to severe dementia. The SIB examines selected aspects of cognitive performance, including elements of attention, orientation, language, memory, visuospatial ability, construction, praxis, and social interaction. The SIB scoring range is from 0 to 100, with lower scores indicating greater cognitive impairment.

The ability of memantine hydrochloride extended-release to produce an overall clinical effect was assessed using a Clinician's Interview Based Impression of Change that required the use of caregiver information, the CIBIC-Plus. The CIBIC-Plus is not a single instrument and is not a standardized instrument like the ADCS-ADL or SIB. Clinical trials for investigational drugs have used a variety of CIBIC formats, each different in terms of depth and structure. As such, results from a CIBIC-Plus reflect clinical experience from the trial or trials in which it was used and cannot be compared directly with the results of CIBIC-Plus evaluations from other clinical trials. The CIBIC-Plus used in this trial was a structured instrument based on a comprehensive evaluation at baseline and subsequent time-points of four domains: general (overall clinical status), functional (including activities of daily living), cognitive, and behavioral. It represents the assessment of a skilled clinician using validated scales based on his/her observation during an interview with the patient, in combination with information supplied by a caregiver familiar with the behavior of the patient over the interval rated. The CIBIC-Plus is scored as a seven point categorical rating, ranging from a score of 1, indicating "marked improvement" to a score of 4, indicating "no change" to a score of 7, indicating "marked worsening." The CIBIC-Plus has not been systematically compared directly to assessments not using information from caregivers (CIBIC) or other global methods.

Study Results

In this study, 677 patients were randomized to one of the following 2 treatments: memantine hydrochloride extended-release 28 mg/day or placebo while still receiving an AChEI (either donepezil, galantamine, or rivastigmine).

Effects on Severe Impairment Battery (SIB)

Figure 1 shows the time course for the change from baseline in SIB score for the two treatment groups completing the 24 weeks of the study. At 24 weeks of treatment, the mean difference in the SIB change scores for the memantine hydrochloride extended-release 28 mg/AChEI-treated (combination therapy) patients compared to the patients on placebo/AChEI (monotherapy) was 2.6 units. Using an LOCF analysis, memantine hydrochloride extended-release 28 mg/AChEI treatment was statistically significantly superior to placebo/AChEI.

Figure 1: Time course of the change from baseline in SIB score for patients completing 24 weeks of treatment.

Figure 2 shows the cumulative percentages of patients from each treatment group who had attained at least the measure of improvement in SIB score shown on the X axis. The curves show that both patients assigned to memantine hydrochloride extended-release 28 mg/AChEI and placebo/AChEI have a wide range of responses, but that the memantine hydrochloride extended-release 28 mg/AChEI group is more likely to show an improvement or a smaller decline.

Figure 2: Cumulative percentage of patients completing 24 weeks of double-blind treatment with specified changes from baseline in SIB scores.

Figure 3 shows the time course for the CIBIC-Plus score for patients in the two treatment groups completing the 24 weeks of the study. At 24 weeks of treatment, the mean difference in the CIBIC-Plus scores for the memantine hydrochloride extended-release 28 mg/AChEI-treated patients compared to the patients on placebo/AChEI was 0.3 units. Using an LOCF analysis, memantine hydrochloride extended-release 28 mg/AChEI treatment was statistically significantly superior to placebo/AChEI.

Figure 3: Time course of the CIBIC-Plus score for patients completing 24 weeks of treatment.

Figure 4 is a histogram of the percentage distribution of CIBIC-Plus scores attained by patients assigned to each of the treatment groups who completed 24 weeks of treatment.

Figure 4: Distribution of CIBIC-Plus ratings at week 24.

16 HOW SUPPLIED/STORAGE AND HANDLING

7 mg Capsule

Size '4' hard gelatin yellow capsule with yellow opaque cap and yellow opaque body, with black imprint "LU" on cap and "O61" on body.

Cartons of 100 extended-release capsules (10 extended-release capsules each blister pack x 10), NDC 0904-6734-61

28 mg Capsule

Size '3' hard gelatin dark green capsule with black imprint "LU" on cap and "O64" on body.

Cartons of 100 extended-release capsules (10 extended-release capsules each blister pack x 10), NDC 0904-6735-61

WARNING: These Unit Dose packages are not child resistant and are Intended for Institutional Use Only. Keep this and all drugs out of the reach of children.

Store memantine hydrochloride extended-release at 25°C (77°F); excursions permitted to 15 to 30°C (59 to 86°F) [see USP Controlled Room Temperature].

17 PATIENT COUNSELING INFORMATION

Advise the patient to read the FDA-approved patient labeling (Patient Information).

• To assure safe and effective use of memantine hydrochloride extended-release, the information and instructions provided in the patient information section should be discussed with patients and caregivers.

• Instruct patients and caregivers to take memantine hydrochloride extended-release only once per day, as prescribed.

• Instruct patients and caregivers that memantine hydrochloride extended-release capsules be swallowed whole. Alternatively, memantine hydrochloride extended-release capsules may be opened and sprinkled on applesauce and the entire contents should be consumed. The capsules should not be divided, chewed or crushed.

• Warn patients not to use any capsules of memantine hydrochloride extended-release that are damaged or show signs of tampering.

• If a patient misses a single dose of memantine hydrochloride extended-release, that patient should not double up on the next dose. The next dose should be taken as scheduled. If a patient fails to take memantine hydrochloride extended-release for several days, dosing should not be resumed without consulting that patient's healthcare professional.

• Advise patients and caregivers that memantine hydrochloride extended-release may cause headache, diarrhea, and dizziness.

LUPIN and the are registered trademarks of Lupin Pharmaceuticals, Inc.

Manufactured for:

Lupin Pharmaceuticals, Inc.

Naples, FL 34108

United States

Manufactured by:

Lupin Limited

Nagpur – 441 108

India

Packaged and Distributed by:

MAJOR® PHARMACEUTICALS

Indianapolis, IN 46268 USA

Refer to package label for Distributor's NDC Number

May 2025

Patient Information

Memantine Hydrochloride [me-MAN-teen HYE-droe-KLOR-ide]

Extended-release Capsules

Rx Only

Read this Patient Information that comes with memantine hydrochloride extended-release capsules before you start taking it and each time you get a refill. There may be new information. This information does not take the place of talking to your doctor about your medical condition or your treatment.

What are memantine hydrochloride extended-release capsules?

Memantine hydrochloride extended-release capsule is a prescription medicine used for the treatment of moderate to severe dementia in people with Alzheimer's disease. Memantine hydrochloride extended-release capsule belongs to a class of medicines called N-methyl-D-aspartate (NMDA) inhibitors.

It is not known if memantine hydrochloride extended-release capsule is safe and effective in children.

Who should not take memantine hydrochloride extended-release capsules?

Do not take memantine hydrochloride extended-release capsules if you are allergic to memantine or any of the other ingredients in memantine hydrochloride extended-release capsules. See the end of this leaflet for a complete list of ingredients in memantine hydrochloride extended-release capsules.

What should I tell my doctor before taking memantine hydrochloride extended-release capsules?

Before you take memantine hydrochloride extended-release capsules, tell your doctor if you:

- have or have had seizures
- have or have had problems passing urine
- have or have had bladder or kidney problems
- have liver problems
- have any other medical conditions
- are pregnant or plan to become pregnant. It is not known if memantine hydrochloride extended-release will harm your unborn baby.
- are breastfeeding or plan to breastfeed. It is not known if memantine passes into your breast milk. Talk to your doctor about the best way to feed your baby if you take memantine hydrochloride extended-release.

Tell your doctor about all the medicines you take, including prescription and nonprescription medicines, vitamins, and herbal supplements.

Taking memantine hydrochloride extended-release capsules with certain other medicines may affect each other. Taking memantine hydrochloride extended-release capsules with other medicines can cause serious side effects.

Especially tell your doctor if you take:

• other NMDA antagonists such as amantadine, ketamine, and dextromethorphan

• medicines that make your urine alkaline such as carbonic anhydrase inhibitors and sodium bicarbonate

Ask your doctor or pharmacist for a list of these medicines, if you are not sure.

Know the medicines you take. Keep a list of them to show your doctor and pharmacist when you get a new medicine.

How should I take memantine hydrochloride extended-release capsules?

- Your doctor will tell you how much memantine hydrochloride extended-release capsules to take and when to take it.
- Your doctor may change your dose if needed.
- Memantine hydrochloride extended-release capsules may be taken with food or without food.
- Memantine hydrochloride extended-release capsules may be opened and sprinkled on applesauce before swallowing, but the contents of the entire capsule should be taken and the dose should not be divided. Except when opened and sprinkled on applesauce, memantine hydrochloride extended-release capsules must be swallowed whole and never crushed, divided or chewed.
- Do not use any capsules of memantine hydrochloride extended-release that are damaged or show signs of tampering.
- If you are currently taking another formulation of memantine, talk to your healthcare professional about how to switch to memantine hydrochloride extended-release capsules.
- If you forget to take one dose of memantine hydrochloride extended-release capsules, do not double up on the next dose. You should take only the next dose as scheduled.
- If you have forgotten to take memantine hydrochloride extended-release capsules for several days, you should not take the next dose until you talk to your doctor.
- If you take too much memantine hydrochloride extended-release capsules call your doctor or poison control center at 1-800-222-1222, or go to the nearest hospital emergency room right away.

What are the possible side effects of memantine hydrochloride extended-release capsules?

Memantine hydrochloride extended-release capsules may cause side effects, including:

The most common side effects of memantine hydrochloride extended-release capsules include:

• headache

• diarrhea

• dizziness

These are not all the possible side effects of memantine hydrochloride extended-release capsules. For more information, ask your doctor or pharmacist.

Call your doctor for medical advice about side effects. You may report side effects to FDA at 1-800-FDA-1088.

You may also report side effects to Lupin Pharmaceuticals, Inc. at 1-800-399-2561 or visit our website at www.lupinpharmaceuticals.com.

How should I store memantine hydrochloride extended-release capsules?

Store memantine hydrochloride extended-release capsules at room temperature between 68°F to 77°F (20°C to 25°C).

Keep memantine hydrochloride extended-release capsules and all medicines out of the reach of children.

What are the ingredients in memantine hydrochloride extended-release capsules?

Active ingredient: memantine hydrochloride USP

Inactive ingredients: ethyl cellulose, gelatin, hypromellose, maize starch, sucrose, talc, titanium dioxide and triethyl citrate in hard gelatin capsules. Additionally, 7 mg strength capsules contain D&C Yellow #10 and FD&C Red #40; 14 mg strength capsules contain D&C Yellow #10, FD&C Blue #1, FD&C Red #40 and iron oxide yellow; 21 mg and 28 mg strength capsules contain FD&C Blue #1 and iron oxide yellow. The capsules are printed with edible ink containing black iron oxide, potassium hydroxide, propylene glycol and shellac.

General information about the safe and effective use of memantine hydrochloride extended-release capsules:

Medicines are sometimes prescribed for purposes other than those listed in a Patient Information leaflet. Do not take memantine hydrochloride extended-release capsules for a condition for which it was not prescribed. Do not give memantine hydrochloride extended-release capsules to other people, even if they have the same condition. It may harm them.

This Patient Information leaflet summarizes the most important information about memantine hydrochloride extended-release capsules. If you would like more information, talk with your doctor. You can ask your doctor or pharmacist for information about memantine hydrochloride extended-release capsules that was written for healthcare professionals.

This Patient Information has been approved by the U.S. Food and Drug Administration.

LUPIN and the are registered trademarks of Lupin Pharmaceuticals, Inc.

Manufactured for:

Lupin Pharmaceuticals, Inc.

Naples, FL 34108

United States

Manufactured by:

Lupin Limited

Nagpur – 441 108

India

Packaged and Distributed by:

MAJOR® PHARMACEUTICALS

Indianapolis, IN 46268 USA

Refer to package label for Distributor's NDC Number

May 2025 ID#: 280608

Package/Label Display Panel

MAJOR®

NDC 0904-6734-61

Unit Dose

Once-Daily

Memantine Hydrochloride

Extended-Release

Capsules

7 mg

100 CAPSULES (10 x 10)

Rx only

Package/Label Display Panel

MAJOR®

PHARMACEUTICALS

NDC 0904-6736-61

Unit Dose

ONCE-DAILY

MEMANTINE

HYDROCHLORIDE

EXTENDED-RELEASE CAPSULES

14 mg

PHARMACIST: DISPENSE WITH

PATIENT INFORMATION LEAFLET

Rx only

100 CAPSULES

Package/Label Display Panel

MAJOR®

PHARMACEUTICALS

NDC 0904-6737-61

Unit Dose

ONCE-DAILY

MEMANTINE

HYDROCHLORIDE

EXTENDED-RELEASE CAPSULES

21 mg

PHARMACIST: DISPENSE WITH

PATIENT INFORMATION LEAFLET

Rx only

100 CAPSULES

Package/Label Display Panel

MAJOR®

NDC 0904-6735-61

Unit Dose

Once-Daily

Memantine Hydrochloride

Extended-Release

Capsules

28 mg

100 CAPSULES (10 x 10)

Rx only